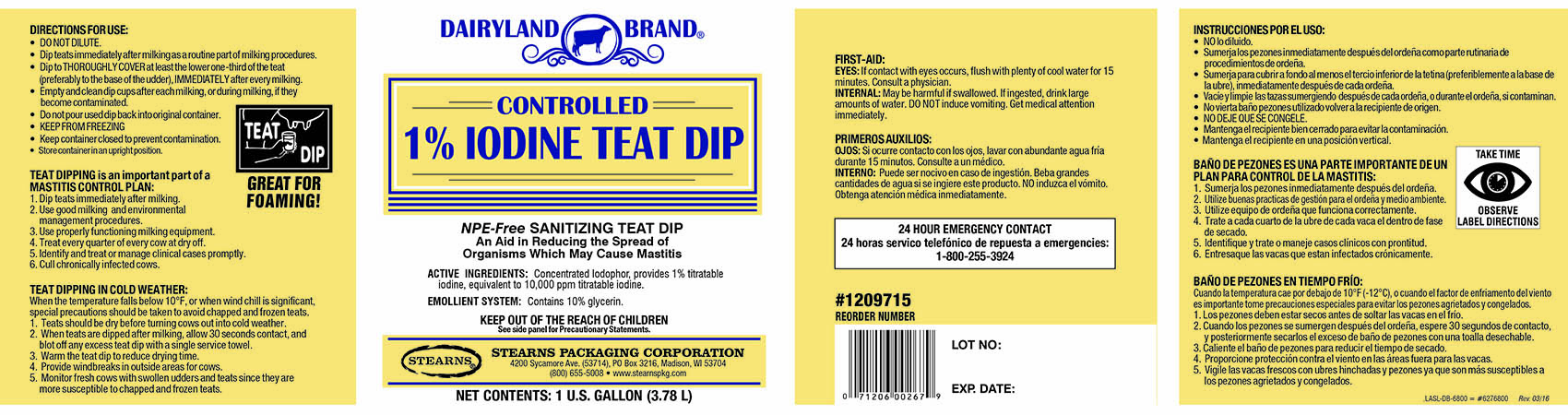 DRUG LABEL: Dairyland Brand Iodine Teat Dip
NDC: 60282-2201 | Form: LIQUID
Manufacturer: Stearns Packaging Corporation
Category: animal | Type: OTC ANIMAL DRUG LABEL
Date: 20251201

ACTIVE INGREDIENTS: IODINE 10 g/1 L
INACTIVE INGREDIENTS: GLYCERIN 100 g/1 L

Controlled 1% Iodine Teat Dip

GENERAL PRECAUTIONS

GREAT FOR FOAMING!

TEAT DIPPING is an important part of a MASTITIS
CONTROL PLAN:

1. Dip teats immediately after milking.
2. Use good milking and environmental management
procedures.
3. Use properly functioning milking equipment.
4. Treat every quarter of every cow at dry off.
5. Identify and treat or manage clinical cases promptly.
6. Cull chronically infected cows.

TEAT DIPPING IN COLD WEATHER:
When the temperature falls below 10 degrees F, or when wind chill is significant, special
precautions should be taken to avoid chapped and frozen teats.

1. Teats should be dry before turning cows out into cold weather.
2. When teats are dipped after milking, allow 30 seconds contact, and blot
off any excess teat dip with a single service towel.
3. Warm the teat dip to reduce drying time.
4. Provide windbreaks in outside areas for cows.
5. Monitor fresh cows with swollen udders and teats since
they are more susceptible to chapped and frozen teats.

DOSAGE AND ADMINISTRATION

TAKE TIME

OBSERVE
LABEL DIRECTIONS

DIRECTIONS FOR USE:

- DO NOT DILUTE.
- Dip teats immediately after milking as a routine part of milking
  procedures.
- Dip to THOROUGHLY COVER at least the lower one-third of the teat
  (preferably to the base of the udder), IMMEDIATELY after every milking.

STORAGE AND HANDLING

- Empty and clean dip cups after each milking, or during milking, if they
  become contaminated.
- Do not pour use dip back into original container.
- KEEP FROM FREEZING
- Keep container closed to prevent contamination.
- Store container in an upright position.

USER SAFETY WARNINGS

FIRST-AID
EYES: If contact with eyes occurs, flush with plenty of cool water for 15
minutes. Consult a physician.
INTERNAL: May be harmful if swallowed. If ingested, drink large amounts
of water or milk. DO NOT induce vomiting. Get medical attention
immediately.

FOR ASSISTANCE WITH MEDICAL
EMERGENCY CONTACT:
CHEM-TEL, 1-800-255-3924

PACKAGE LABEL

DAIRYLAND BRAND

CONTROLLED
IODINE TEAT DIP

SANITIZING TEAT DIP
An Aid in Reducing the Spread of
Organisms WhichMay Cause Mastitis

ACTIVE INGREDIENTS:
Concentrated Iodophor, containing Nonylphenol, ethoxylated iodine complex.
(provides 1% titratable iodine, equivalent to 10,000 ppm titratable iodine)

EMOLLIENT SYSTEM contains 10% glycerin.

KEEP OUT OF THE REACH OF CHILDREN
CAUTION: HARMFUL IF SWALLOWED / EYE IRRITANT

STEARNS PACKAGING CORPORATION
4200 Sycamore Avenue • Madison, WI 53714

NET CONTENTS: 1 U.S. FL. GALLON (3.78 L)